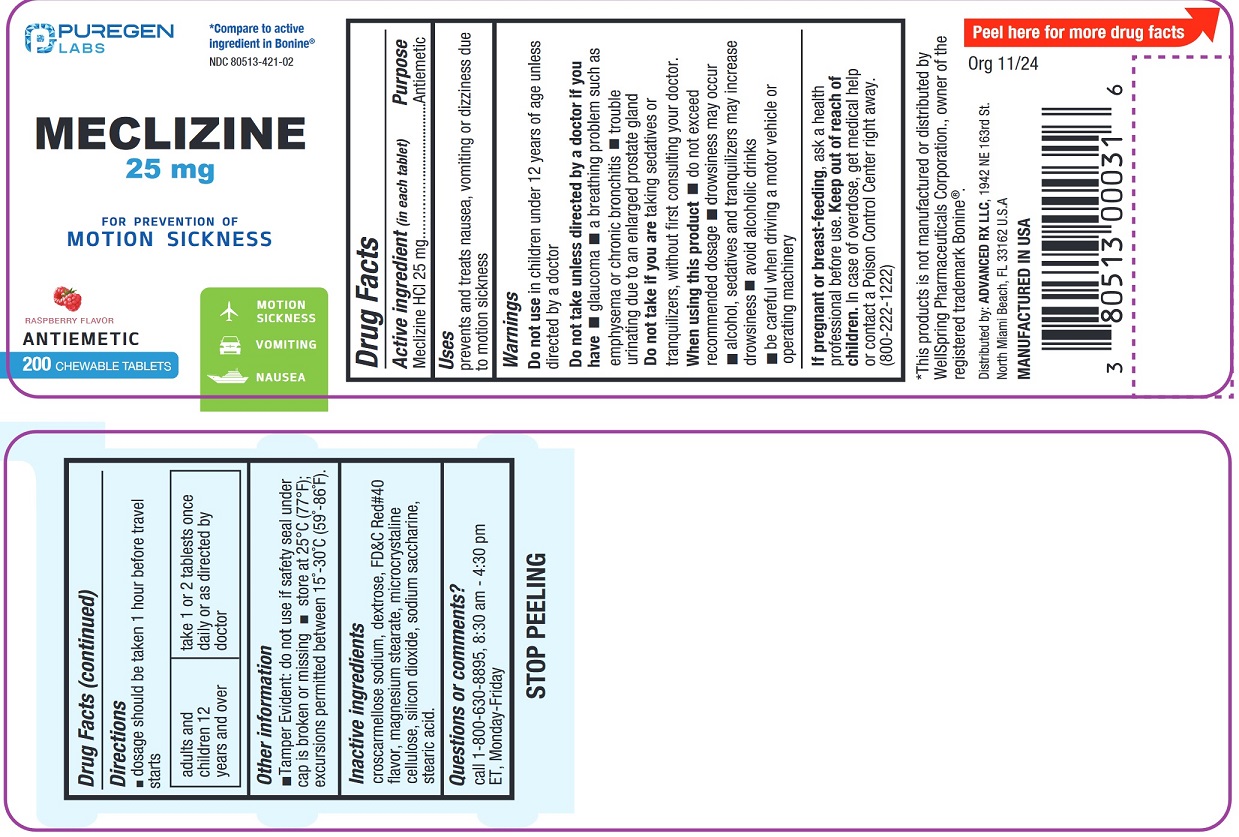 DRUG LABEL: Meclizine
NDC: 80513-421 | Form: TABLET, CHEWABLE
Manufacturer: Advanced Rx LLC
Category: otc | Type: HUMAN OTC DRUG LABEL
Date: 20241127

ACTIVE INGREDIENTS: MECLIZINE HYDROCHLORIDE 25 mg/1 1
INACTIVE INGREDIENTS: CROSCARMELLOSE SODIUM; DEXTROSE; FD&C RED NO. 40; MAGNESIUM STEARATE; CELLULOSE, MICROCRYSTALLINE; SILICON DIOXIDE; SACCHARIN SODIUM; STEARIC ACID; RASPBERRY

Active ingredient (in each tablet)

Meclizine HCl 25 mg

Purpose

Antiemetic

Uses

prevents and treats nausea, vomiting or dizziness associated with motion sickness

Warnings

Do not use in children under 12 years of age unless directed by a doctor.

Do not take unless directed by a doctor if you have

- glaucoma
- a breathing problem such as emphysema or chronic bronchitis
- trouble urinating due to an enlarged prostate gland

Do not take this product if you aretaking sedatives or tranquilizers, without first consulting your doctor.

When using this product

- do not exceed recommended dosage
- drowsiness may occures
- alcohol, sedatives, and tranquilizers may increase drowsiness
- avoid alcoholic drinks
- be careful when driving a motor vehicle or operating machinery

If pregnant or breast-feeding,

ask a health professional before use.

Keep out of reach of children.

In case of overdose, get medical help or contact a Poison Control Center right away (1-800-222-1222)

Directions

- doage should be taken 1 hour before travel starts

adults and children 12 years and over | take 1 or 2 tablets once daily or as directed by doctor

Other information

- Tamper Evident:do not use if safety seal under cap is broken or missing
- store at 25°C (77°F); excursions permitted between 15°-30°C (59°-86°F).

Inactive ingredients

croscarmellose sodium, dextrose, FD&C Red#40, flavor, magnesium stearate, microcrystalline cellulose, silicon dioxide, sodium saccharine, stearic acid.

Questions or comments?

call 1-800-630-8895, 8:30 am - 4.30 pm ET, Monday-Friday

PACKAGE LABEL

NDC 80513-421-02

*Compare to the active ingredient in Bonine®

Meclizine HCl 25 mg

Raspberry Flavor

Antiemetic

• Motion Sickness

• Vomiting

• Nausea

200 CHEWABLE TABLETS

*This product is not manufactured or distributed by WellSpring Pharmaceuticals Corporation., owner of the registered trademark Bonine®

Distributed by:

ADVANCED RX LLC,

1942 NE 163rd St

North Miami Beach, FL 33162 U.S.A.

Manufactured in the USA